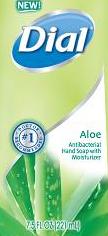 DRUG LABEL: Dial Aloe Antibacterial Soap
NDC: 54340-797 | Form: SOLUTION
Manufacturer: The Dial Corporation
Category: otc | Type: HUMAN OTC DRUG LABEL
Date: 20100127

ACTIVE INGREDIENTS: TRICLOSAN 0.15 mL/1000 mL

Drug Facts

Active Ingredient - TRICLOSAN 0.15%

Purpose - Antibacterial

PURPOSE

Uses - For handwashing to decrease bacteria on the skin

Warnings - For external use only

When using this product avoid contact with eyes. In case of eye contact, flush with water.

Stop use and ask a doctor if irritation and redness develops.

Keep out of reach of children. If swallowed, get medical help or contact a Poison Control Center right away.

Directions: Pump into hands, wet as needed. Lather vigorously for at lest 15 seconds. Wash skin, rinse thoroughly and dry.

INACTIVE INGREDIENT

Inactive Ingredients: Water, Sodium Laureth Sulfate, Cocamidopropyl Betaine, Sodium Chloride, Cocamidopropyl Hydroxysultaine, Glycerin, Fragrance, Glycol Distearate, Steareth-4, Aloe-Barbadensis Leaf Juice, Polyquaternium-7, PPG-2 Hydroxyethyl Coco/Isostearamide, DMDM Hydantoin, Tetrasodium EDTA, Citric Acid, Yellow 5, Blue 1

Questions? 1-800-258-DIAL (3425)